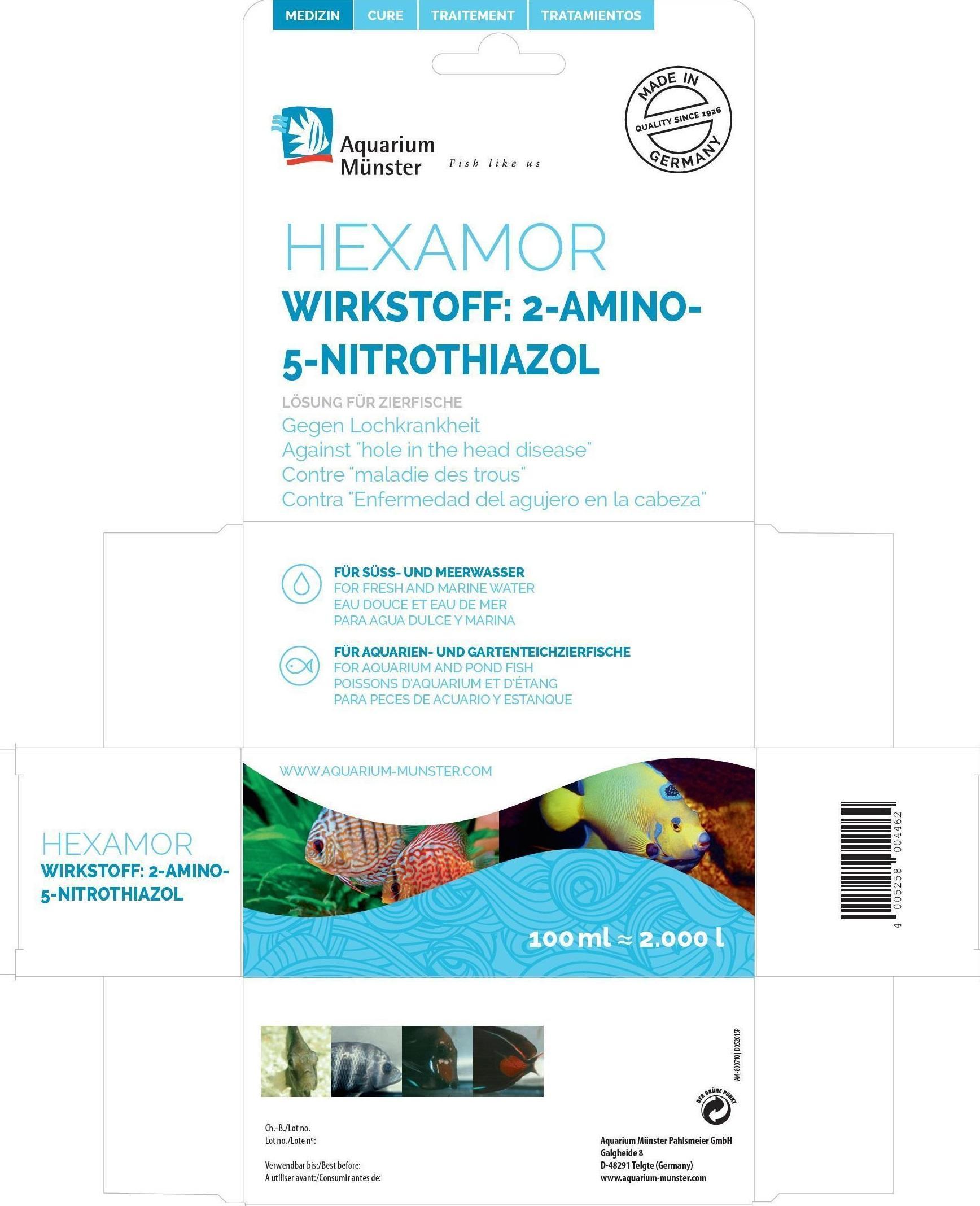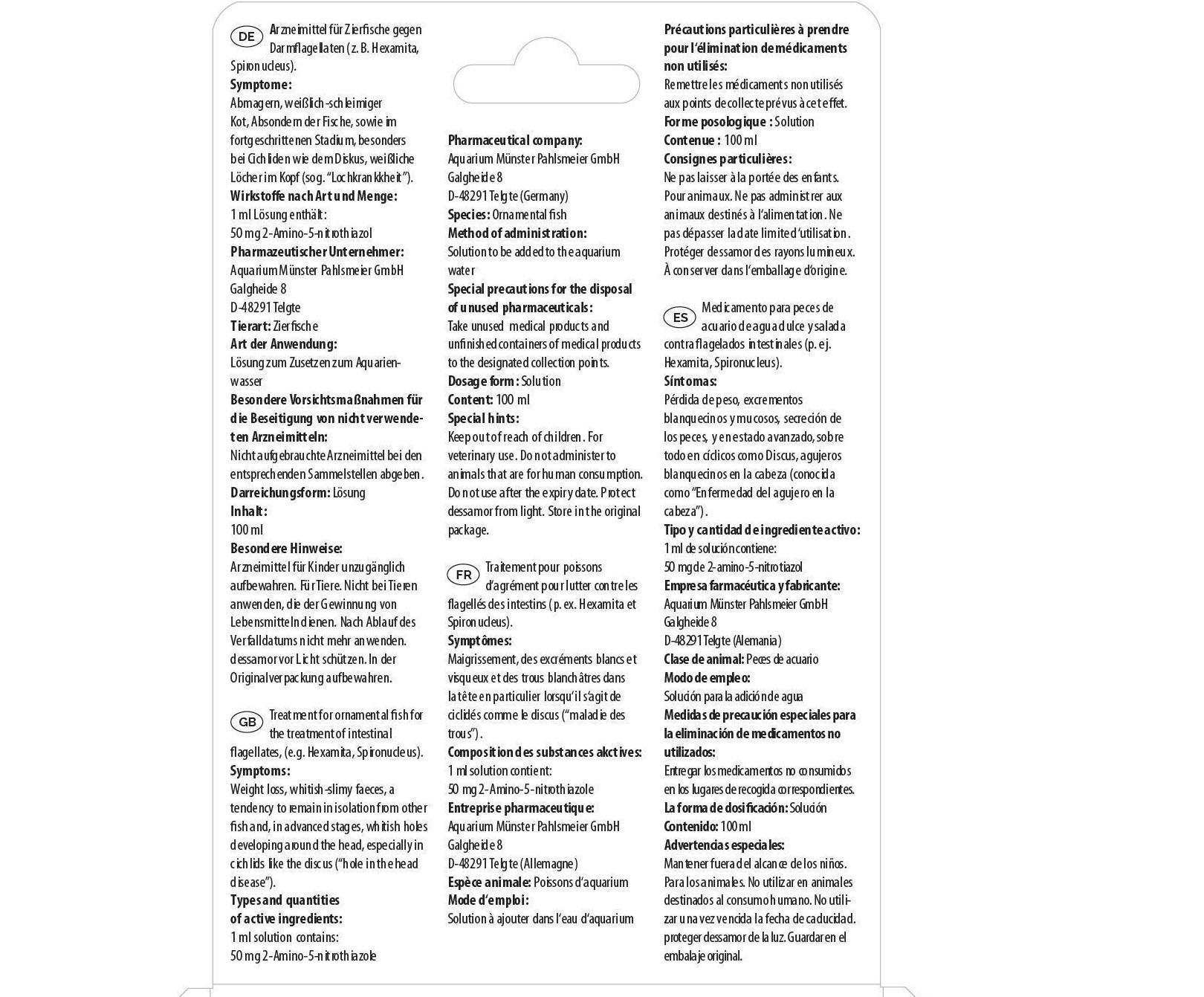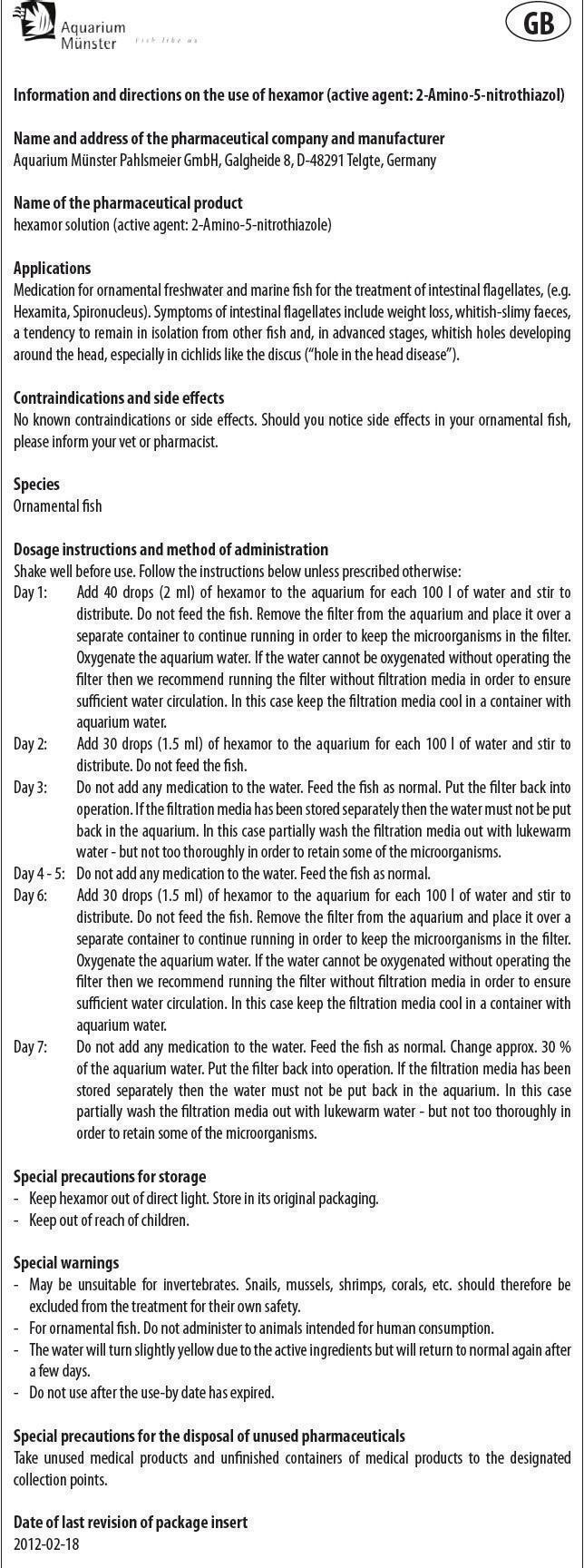 DRUG LABEL: Hexamor
NDC: 86052-009 | Form: SOLUTION
Manufacturer: Aquarium Muenster Pahlsmeier GmbH
Category: animal | Type: OTC ANIMAL DRUG LABEL
Date: 20240419

ACTIVE INGREDIENTS: 2-AMINO-5-NITROTHIAZOLE 50 mg/1 mL

Hexamor

Information and directions on the use of hexamor (active agent: 2-Amino-5-nitrothiazol)

Name and address of the pharmaceutical company and manufacturer
Aquarium Münster Pahlsmeier GmbH, Galgheide 8, D-48291 Telgte, Germany

Name of the pharmaceutical product
hexamor solution (active agent: 2-Amino-5-nitrothiazole)

Applications

Medication for ornamental freshwater and marine fish for the treatment of intestinal flagellates, (e.g. Hexamita, Spironucleus). Symptoms of intestinal flagellates include weight loss, whitish-slimy faeces, a tendency to remain in isolation from other fish and, in advanced stages, whitish holes developing around the head, especially in cichlids like the discus (“hole in the head disease”).

Types and quantities of active ingredients:

1 ml solution contains:
50 mg 2-Amino-5-nitrothiazole

Contraindications and side effects

No known contraindications or side effects. Should you notice side effects in your ornamental fish, please inform your vet or pharmacist.

Species

Ornamental fish

Dosage instructions and method of administration

Shake well before use. Follow the instructions below unless prescribed otherwise:
Day 1: Add 40 drops (2 ml) of hexamor to the aquarium for each 100 l of water and stir to distribute. Do not feed the fish. Remove the filter from the aquarium and place it over a separate container to continue running in order to keep the microorganisms in the filter. Oxygenate the aquarium water. If the water cannot be oxygenated without operating the filter then we recommend running the filter without filtration media in order to ensure sufficient water circulation. In this case keep the filtration media cool in a container with aquarium water.
Day 2: Add 30 drops (1.5 ml) of hexamor to the aquarium for each 100 l of water and stir to distribute. Do not feed the fish.
Day 3: Do not add any medication to the water. Feed the fish as normal. Put the filter back into operation. If the filtration media has been stored separately then the water must not be put back in the aquarium. In this case partially wash the filtration media out with lukewarm
water - but not too thoroughly in order to retain some of the microorganisms.
Day 4 - 5: Do not add any medication to the water. Feed the fish as normal.
Day 6: Add 30 drops (1.5 ml) of hexamor to the aquarium for each 100 l of water and stir to distribute. Do not feed the fish. Remove the filter from the aquarium and place it over a separate container to continue running in order to keep the microorganisms in the filter. Oxygenate the aquarium water. If the water cannot be oxygenated without operating the filter then we recommend running the filter without filtration media in order to ensure sufficient water circulation. In this case keep the filtration media cool in a container with aquarium water.
Day 7: Do not add any medication to the water. Feed the fish as normal. Change approx. 30 % of the aquarium water. Put the filter back into operation. If the filtration media has been stored separately then the water must not be put back in the aquarium. In this case partially wash the filtration media out with lukewarm water - but not too thoroughly in order to retain some of the microorganisms.

Special precautions for storage

- Keep hexamor out of direct light. Store in its original packaging

- Keep out of reach of children.

Special warnings

- May be unsuitable for invertebrates. Snails, mussels, shrimps, corals, etc. should therefore be excluded from the treatment for their own safety.
- For ornamental fish. Do not administer to animals intended for human consumption.
- The water will turn slightly yellow due to the active ingredients but will return to normal again after a few days.
- Do not use after the use-by date has expired.

Special precautions for the disposal of unused pharmaceuticals

Take unused medical products and unfinished containers of medical products to the designated collection points.